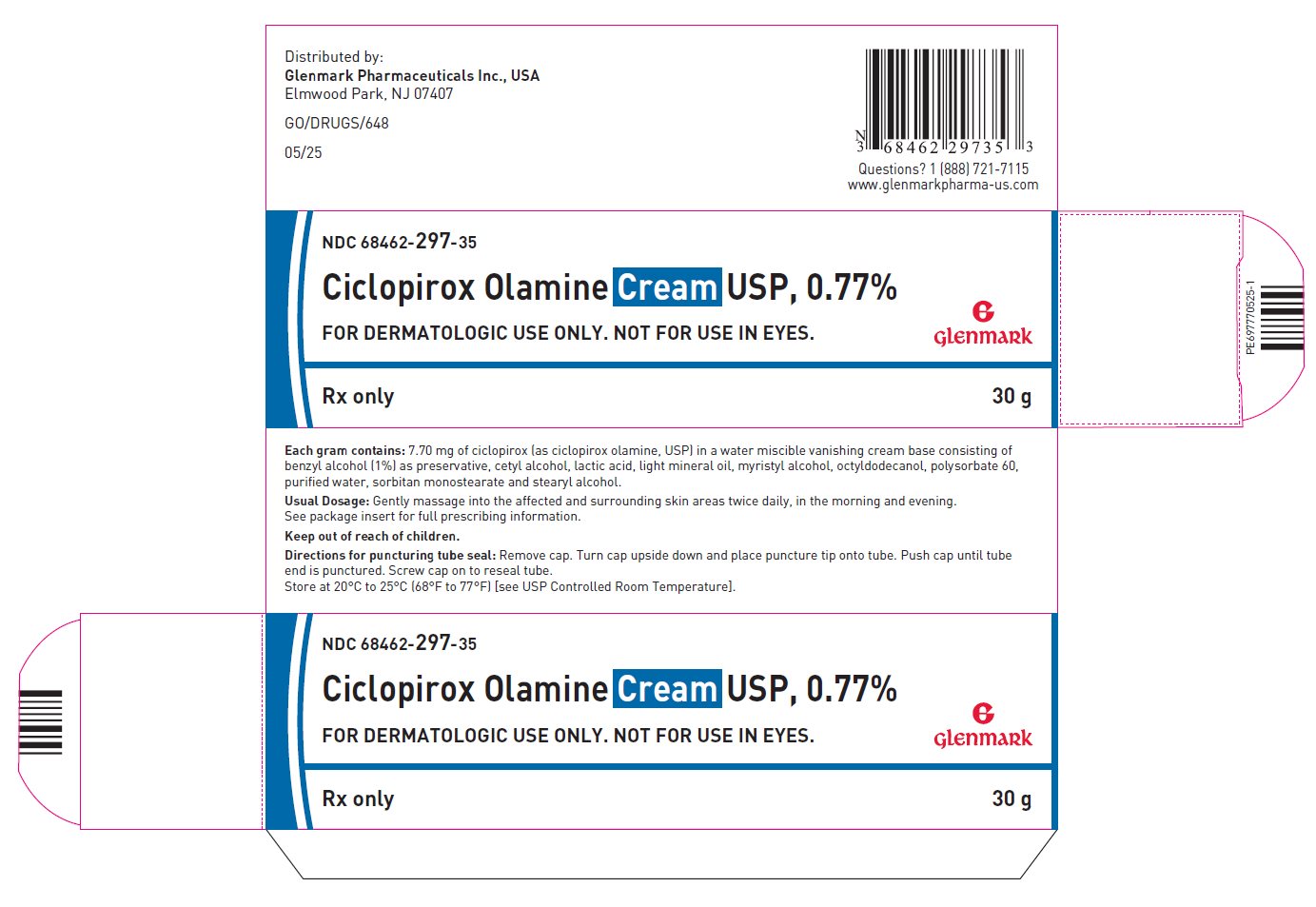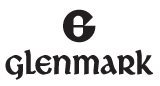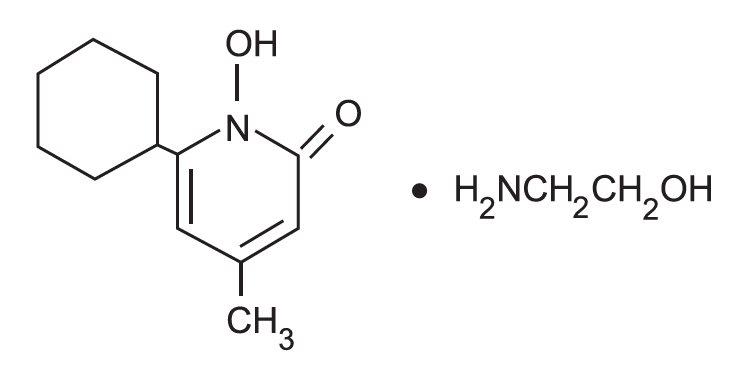 DRUG LABEL: Ciclopirox Olamine
NDC: 68462-297 | Form: CREAM
Manufacturer: Glenmark Pharmaceuticals Inc., USA
Category: prescription | Type: HUMAN PRESCRIPTION DRUG LABEL
Date: 20260122

ACTIVE INGREDIENTS: CICLOPIROX OLAMINE 7.7 mg/1 g
INACTIVE INGREDIENTS: CETYL ALCOHOL; LIGHT MINERAL OIL; OCTYLDODECANOL; STEARYL ALCOHOL; POLYSORBATE 60; MYRISTYL ALCOHOL; SORBITAN MONOSTEARATE; LACTIC ACID, UNSPECIFIED FORM; BENZYL ALCOHOL; WATER

Ciclopirox Olamine Cream USP, 0.77%

FOR DERMATOLOGIC USE ONLY.
NOT FOR USE IN EYES.

Rx Only

DESCRIPTION

Ciclopirox olamine cream, USP, 0.77% is for topical use. Each gram of ciclopirox olamine cream, USP contains 7.70 mg of ciclopirox (as ciclopirox olamine USP) in a water miscible vanishing cream base consisting of benzyl alcohol (1%) as preservative, cetyl alcohol, lactic acid, light mineral oil, myristyl alcohol, octyldodecanol, polysorbate 60, purified water, sorbitan monostearate and stearyl alcohol.

Ciclopirox olamine cream, USP contains a synthetic, broad-spectrum, antifungal agent ciclopirox (as ciclopirox olamine USP). The chemical name is 6-cyclohexyl-1-hydroxy-4-methyl-2(1H)-pyridone, 2 -aminoethanol salt.

The CAS Registry Number is 41621-49-2. The chemical structure is:

CLINICAL PHARMACOLOGY

Mechanism of Action

Ciclopirox is a hydroxypyridone antifungal agent that acts by chelation of polyvalent cations (Fe^3+ or Al^3+), resulting in the inhibition of the metal-dependent enzymes that are responsible for the degradation of peroxides within the fungal cell.

Pharmacokinetics

Pharmacokinetic studies in men with tagged ciclopirox solution in polyethylene glycol 400 showed an average of 1.3% absorption of the dose when it was applied topically to 750 cm^2 on the back followed by occlusion for 6 hours. The biological half-life was 1.7 hours and excretion occurred via the kidney. Two days after application only 0.01% of the dose applied could be found in the urine. Fecal excretion was negligible.

Penetration studies in human cadaverous skin from the back, with ciclopirox olamine cream with tagged ciclopirox showed the presence of 0.8 to 1.6% of the dose in the stratum corneum 1.5 to 6 hours after application. The levels in the dermis were still 10 to 15 times above the minimum inhibitory concentrations.

Autoradiographic studies with human cadaverous skin showed that ciclopirox penetrates into the hair and through the epidermis and hair follicles into the sebaceous glands and dermis, while a portion of the drug remains in the stratum corneum.

Draize Human Sensitization Assay, 21-Day Cumulative Irritancy study, Phototoxicity study, and Photo-Draize study conducted in a total of 142 healthy male subjects showed no contact sensitization of the delayed hypersensitivity type, no irritation, no phototoxicity, and no photo-contact sensitization due to ciclopirox olamine cream.

INDICATIONS AND USAGE

Ciclopirox olamine cream is indicated for the topical treatment of the following dermal infections: tinea pedis, tinea cruris, and tinea corporis due to Trichophyton rubrum, Trichophyton mentagrophytes, Epidermophyton floccosum, and Microsporum canis; candidiasis (moniliasis) due to Candida albicans; and tinea (pityriasis) versicolor due to Malassezia furfur.

CONTRAINDICATIONS

Ciclopirox olamine cream is contraindicated in individuals who have shown hypersensitivity to any of its components.

WARNINGS

Ciclopirox olamine cream is not for ophthalmic use.
Keep out of reach of children.

PRECAUTIONS

If a reaction suggesting sensitivity or chemical irritation should occur with the use of ciclopirox olamine cream, treatment should be discontinued and appropriate therapy instituted.

Information for Patients

The patient should be told to:

1. Use the medication for the full treatment time even though symptoms may have improved and notify the physician if there is no improvement after four weeks.
2. Inform the physician if the area of application shows signs of increased irritation (redness, itching, burning, blistering, swelling, or oozing) indicative of possible sensitization.
3. Avoid the use of occlusive wrappings or dressings.

Carcinogenesis, Mutagenesis, Impairment of Fertility

A 104-week dermal carcinogenicity study in mice was conducted with ciclopirox cream applied at doses up to 1.93% (100 mg/kg/day or 300 mg/m^2/day). No increase in drug related neoplasms was noted when compared to control.

The following in vitro genotoxicity tests have been conducted with ciclopirox: evaluation of gene mutation in the Ames Salmonella and E. coli assays (negative); chromosome aberration assays in V79 Chinese hamster lung fibroblast cells, with and without metabolic activation (positive); chromosome aberration assays in V79 Chinese hamster lung fibroblast cells in the presence of supplemental Fe^3+, with and without metabolic activation (negative); gene mutation assays in the HGPRT-test with V79 Chinese hamster lung fibroblast cells (negative); and a primary DNA damage assay (i.e., unscheduled DNA synthesis assay in A549 human cells) (negative). An in vitro cell transformation assay in BALB/c 3T3 cells was negative for cell transformation. In an in vivo Chinese hamster bone marrow cytogenetic assay, ciclopirox was negative for chromosome aberrations at a dosage of 5000 mg/kg body weight.

A combined oral fertility and embryofetal developmental study was conducted in rats with ciclopirox olamine. No effect on fertility or reproductive performance was noted at the highest dose tested of 3.85 mg/kg/day ciclopirox (approximately 1.2 times the maximum recommended human dose based on body surface area comparisons).

Pregnancy

Teratogenic Effects: Pregnancy Category B

There are no adequate or well-controlled studies in pregnant women. Therefore, ciclopirox cream should be used during pregnancy only if the potential benefit justifies the potential risk to the fetus.

Oral embryofetal developmental studies were conducted in mice, rats, rabbits and monkeys. Ciclopirox or ciclopirox olamine was orally administered during the period of organogenesis. No maternal toxicity, embryotoxicity or teratogenicity were noted at the highest doses of 77, 125, 80 and 38.5 mg/kg/day ciclopirox in mice, rats, rabbits and monkeys, respectively (approximately 11, 37, 51 and 24 times the maximum recommended human dose based on body surface area comparisons, respectively).

Dermal embryofetal developmental studies were conducted in rats and rabbits with ciclopirox olamine dissolved in PEG 400. Ciclopirox olamine was topically administered during the period of organogenesis. No maternal toxicity, embryotoxicity or teratogenicity were noted at the highest doses of 92 mg/kg/day and 77 mg/kg/day ciclopirox in rats and rabbits, respectively (approximately 27 and 49 times the maximum recommended human dose based on body surface area comparisons, respectively).

Nursing Mothers

It is not known whether this drug is excreted in human milk. Because many drugs are excreted in human milk, caution should be exercised when ciclopirox olamine cream is administered to a nursing woman.

Pediatric Use

Safety and effectiveness in pediatric patients below the age of 10 years have not been established.

ADVERSE REACTIONS

In all controlled clinical studies with 514 patients using ciclopirox olamine cream and in 296 patients using the vehicle cream, the incidence of adverse reactions was low. This included pruritus at the site of application in one patient and worsening of the clinical signs and symptoms in another patient using ciclopirox olamine cream and burning in one patient and worsening of the clinical signs and symptoms in another patient using the vehicle cream.

DOSAGE AND ADMINISTRATION

Gently massage ciclopirox olamine cream into the affected and surrounding skin areas twice daily, in the morning and evening. Clinical improvement with relief of pruritus and other symptoms usually occurs within the first week of treatment. If a patient shows no clinical improvement after four weeks of treatment with ciclopirox olamine cream, the diagnosis should be redetermined. Patients with tinea versicolor usually exhibit clinical and mycological clearing after two weeks of treatment.

HOW SUPPLIED

Ciclopirox olamine cream USP, 0.77% is supplied in 15 grams (NDC 68462-297-17), 30 grams (NDC 68462-297-35) and 90 grams (NDC 68462-297-92) tubes.

STORAGE AND HANDLING

Store at 20°C to 25°C (68°F to 77°F) [see USP Controlled Room Temperature].

Distributed by:

Glenmark Pharmaceuticals Inc., USA
Elmwood Park, NJ 07407

Questions? 1 (888) 721-7115
www.glenmarkpharma-us.com

May 2025

Principle Display Panel

NDC 68462-297-35
Ciclopirox Olamine Cream USP, 0.77%
For dermatologic use only. Not for use in eyes.